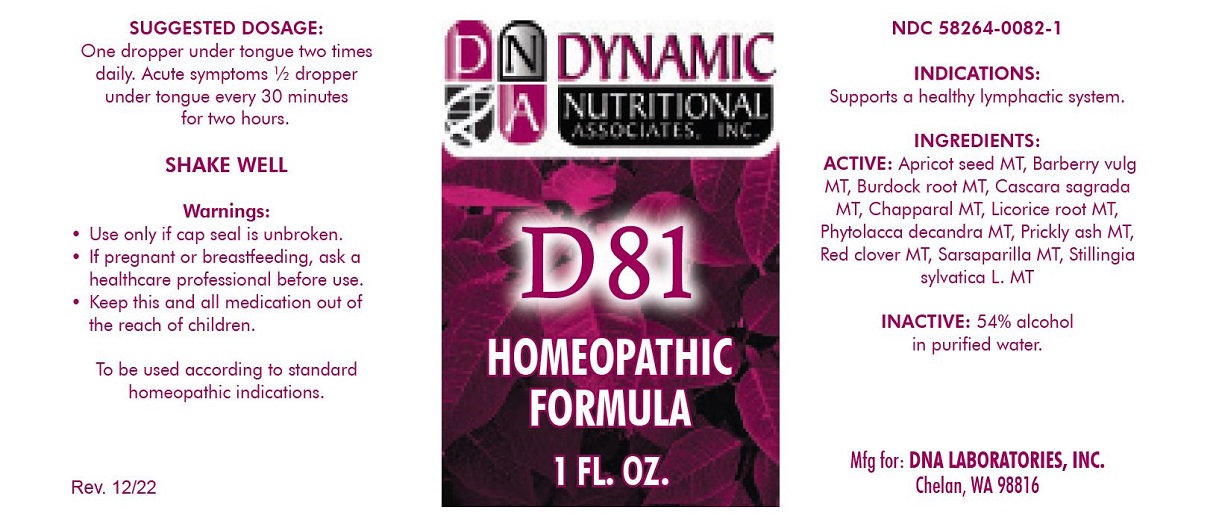 DRUG LABEL: D81
NDC: 58264-0082 | Form: SOLUTION
Manufacturer: DNA Labs, Inc.
Category: homeopathic | Type: HUMAN OTC DRUG LABEL
Date: 20250113

ACTIVE INGREDIENTS: PASSIFLORA INCARNATA WHOLE 1 [hp_X]/1 mL; SMILAX ORNATA WHOLE 1 [hp_X]/1 mL; PHYTOLACCA AMERICANA ROOT 1 [hp_X]/1 mL; STILLINGIA SYLVATICA ROOT 1 [hp_X]/1 mL; TRIFOLIUM PRATENSE WHOLE 1 [hp_X]/1 mL; ARCTIUM LAPPA WHOLE 1 [hp_X]/1 mL; PRUNUS DULCIS WHOLE 1 [hp_X]/1 mL; FRANGULA PURSHIANA BARK 1 [hp_X]/1 mL; BERBERIS VULGARIS WHOLE 1 [hp_X]/1 mL; GLYCYRRHIZA GLABRA WHOLE 1 [hp_X]/1 mL; LARREA DIVARICATA WHOLE 1 [hp_X]/1 mL
INACTIVE INGREDIENTS: ALCOHOL; WATER

D-81

NDC 58264-0082-1

INDICATIONS

PURPOSE

Supports a healthy lymphactic system.

INGREDIENTS

INACTIVE INGREDIENT

Xanthoxylum Ø, Sarsaparilla Ø, Phytolacca Ø, Stillingia Ø, Trifolium pratense Ø, Arctium lappa Ø, Amygdalus Ø, Cascara sagrada Ø, Berberis vulgaris Ø, Glycyrrhiza glabra Ø, Larrea divaricata Ø, 54% alcohol in purified water.

SUGGESTED DOSAGE

One dropper full under the tongue two times daily. In acute conditions 5-10 drops under the tongue every 20-30 minutes.

STORAGE AND HANDLING

SHAKE WELL

Warnings

- Use only if cap seal is unbroken.

PREGNANCY OR BREAST FEEDING

- As with drugs if you are pregnant or nursing a baby seek professional advice before using this product.

KEEP OUT OF REACH OF CHILDREN

- Keep this and all medication out of the reach of children.

To be used according to standard homeopathic indications.

PRINCIPAL DISPLAY PANEL - 1 FL. OZ. Bottle Label

DYNAMIC
NUTRITIONAL
ASSOCIATES, INC.

D-81

HOMEOPATHIC FORMULA

1 FL. OZ.